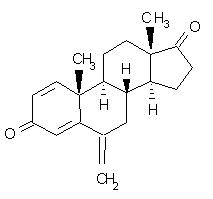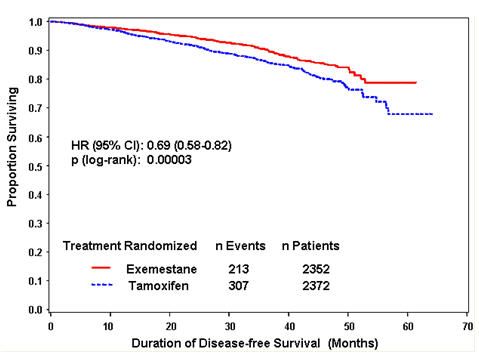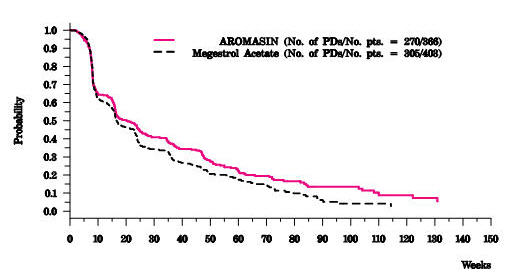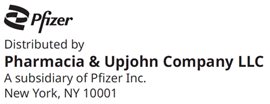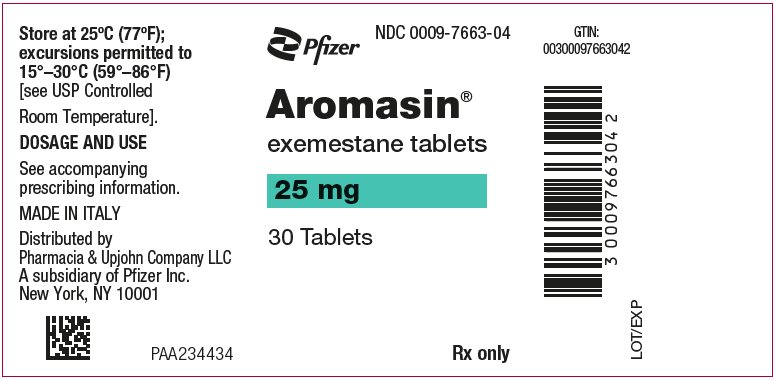 DRUG LABEL: Aromasin
NDC: 0009-7663 | Form: TABLET
Manufacturer: Pharmacia & Upjohn Company LLC
Category: prescription | Type: HUMAN PRESCRIPTION DRUG LABEL
Date: 20251224

ACTIVE INGREDIENTS: EXEMESTANE 25 mg/1 1
INACTIVE INGREDIENTS: MANNITOL; CROSPOVIDONE (120 .MU.M); POLYSORBATE 80; HYPROMELLOSE, UNSPECIFIED; SILICON DIOXIDE; MICROCRYSTALLINE CELLULOSE; MAGNESIUM STEARATE; POLYETHYLENE GLYCOL 6000; SUCROSE; MAGNESIUM CARBONATE; TITANIUM DIOXIDE; METHYLPARABEN; POLYVINYL ALCOHOL, UNSPECIFIED; SODIUM STARCH GLYCOLATE TYPE A POTATO

HIGHLIGHTS OF PRESCRIBING INFORMATION

These highlights do not include all the information needed to use AROMASIN safely and effectively. See full prescribing information for AROMASIN.
AROMASIN® (exemestane) tablets, for oral use
Initial U.S. Approval: 1999

1 INDICATIONS AND USAGE

AROMASIN is an aromatase inhibitor indicated for:

- adjuvant treatment of postmenopausal women with estrogen-receptor positive early breast cancer who have received two to three years of tamoxifen and are switched to AROMASIN for completion of a total of five consecutive years of adjuvant hormonal therapy (14.1).
- treatment of advanced breast cancer in postmenopausal women whose disease has progressed following tamoxifen therapy (14.2).

2 DOSAGE AND ADMINISTRATION

Recommended Dose: One 25 mg tablet once daily after a meal (2.1).

3 DOSAGE FORMS AND STRENGTHS

Tablets: 25 mg (3)

4 CONTRAINDICATIONS

Patients with a known hypersensitivity to the drug or to any of the excipients (4).

5 WARNINGS AND PRECAUTIONS

- Reductions in bone mineral density (BMD) over time are seen with exemestane use (5.1).
- Routine assessment of 25-hydroxy vitamin D levels prior to the start of aromatase inhibitor treatment should be performed (5.2).
- Embryo-Fetal Toxicity: Can cause fetal harm. Advise females of reproductive potential of the potential risk to a fetus and to use effective contraception (5.6, 8.1, 8.3).

6 ADVERSE REACTIONS

- Early breast cancer: Adverse reactions occurring in ≥10% of patients in any treatment group (AROMASIN vs. tamoxifen) were hot flushes (21% vs. 20%), fatigue (16% vs. 15%), arthralgia (15% vs. 9%), headache (13% vs. 11%), insomnia (12% vs. 9%), and increased sweating (12% vs. 10%). Discontinuation rates due to AEs were similar between AROMASIN and tamoxifen (6% vs. 5%). Incidences of cardiac ischemic events (myocardial infarction, angina, and myocardial ischemia) were AROMASIN 1.6%, tamoxifen 0.6%. Incidence of cardiac failure: AROMASIN 0.4%, tamoxifen 0.3% (6, 6.1).
- Advanced breast cancer: Most common adverse reactions were mild to moderate and included hot flushes (13% vs. 5%), nausea (9% vs. 5%), fatigue (8% vs. 10%), increased sweating (4% vs. 8%), and increased appetite (3% vs. 6%) for AROMASIN and megestrol acetate, respectively (6, 6.1).

To report SUSPECTED ADVERSE REACTIONS, contact Pfizer Inc at 1-800-438-1985 or FDA at 1-800-FDA-1088 or www.fda.gov/medwatch.

7 DRUG INTERACTIONS

Strong CYP 3A4 inducers: Concomitant use of strong CYP 3A4 inducers decreases exemestane exposure. Increase the AROMASIN dose to 50 mg (2.2, 7).

8 USE IN SPECIFIC POPULATIONS

Lactation: Advise not to breastfeed (8.2).

FULL PRESCRIBING INFORMATION

1 INDICATIONS AND USAGE

1.1 Adjuvant Treatment of Postmenopausal Women

AROMASIN is indicated for adjuvant treatment of postmenopausal women with estrogen-receptor positive early breast cancer who have received two to three years of tamoxifen and are switched to AROMASIN for completion of a total of five consecutive years of adjuvant hormonal therapy [see Clinical Studies (14.1)].

1.2 Advanced Breast Cancer in Postmenopausal Women

AROMASIN is indicated for the treatment of advanced breast cancer in postmenopausal women whose disease has progressed following tamoxifen therapy [see Clinical Studies (14.2)].

2 DOSAGE AND ADMINISTRATION

2.1 Recommended Dose

The recommended dose of AROMASIN in early and advanced breast cancer is one 25 mg tablet once daily after a meal.

- adjuvant treatment of postmenopausal women with estrogen-receptor positive early breast cancer who have received two to three years of tamoxifen and are switched to AROMASIN for completion of a total of five consecutive years of adjuvant hormonal therapy.
- the treatment of advanced breast cancer in postmenopausal women whose disease has progressed following tamoxifen therapy.

2.2 Dose Modifications

Concomitant use of strong CYP 3A4 inducers decreases exemestane exposure, For patients receiving AROMASIN with a strong CYP 3A4 inducer such as rifampicin or phenytoin, the recommended dose of AROMASIN is 50 mg once daily after a meal [see Drug Interactions (7) and Clinical Pharmacology (12.3)].

3 DOSAGE FORMS AND STRENGTHS

AROMASIN Tablets are round, biconvex, and off-white to slightly gray. Each tablet contains 25 mg of exemestane. The tablets are printed on one side with the number "7663" in black.

4 CONTRAINDICATIONS

AROMASIN is contraindicated in patients with a known hypersensitivity to the drug or to any of the excipients.

5 WARNINGS AND PRECAUTIONS

5.1 Reductions in Bone Mineral Density (BMD)

Reductions in bone mineral density (BMD) over time are seen with exemestane use. Table 1 describes changes in BMD from baseline to 24 months in patients receiving exemestane compared to patients receiving tamoxifen (IES) or placebo (027). Concomitant use of bisphosphonates, vitamin D supplementation, and calcium was not allowed.

Table 1. Percent Change in BMD from Baseline to 24 months, Exemestane vs. Control^1
 | IES |  | 027
BMD | Exemestane N=29 | Tamoxifen^1 N=38 | Exemestane N=59 | Placebo^1 N=65
Lumbar spine (%) | -3.1 | -0.2 | -3.5 | -2.4
Femoral neck (%) | -4.2 | -0.3 | -4.6 | -2.6

During adjuvant treatment with exemestane, women with osteoporosis or at risk of osteoporosis should have their bone mineral density formally assessed by bone densitometry at the commencement of treatment. Monitor patients for bone mineral density loss and treat as appropriate.

5.2 Vitamin D Assessment

Routine assessment of 25-hydroxy vitamin D levels prior to the start of aromatase inhibitor treatment should be performed, due to the high prevalence of vitamin D deficiency in women with early breast cancer (EBC). Women with vitamin D deficiency should receive supplementation with vitamin D.

5.3 Administration with Estrogen-Containing Agents

AROMASIN should not be coadministered with systemic estrogen-containing agents as these could interfere with its pharmacologic action.

5.4 Laboratory Abnormalities

In patients with early breast cancer, the incidence of hematological abnormalities of Common Toxicity Criteria (CTC) grade ≥1 was lower in the exemestane treatment group, compared with tamoxifen. Incidence of CTC grade 3 or 4 abnormalities was low (approximately 0.1%) in both treatment groups. Approximately 20% of patients receiving exemestane in clinical studies in advanced breast cancer experienced CTC grade 3 or 4 lymphocytopenia. Of these patients, 89% had a pre-existing lower grade lymphopenia. Forty percent of patients either recovered or improved to a lesser severity while on treatment. Patients did not have a significant increase in viral infections, and no opportunistic infections were observed. Elevations of serum levels of AST, ALT, alkaline phosphatase, and gamma glutamyl transferase >5 times the upper value of the normal range (i.e., ≥ CTC grade 3) have been rarely reported in patients treated for advanced breast cancer but appear mostly attributable to the underlying presence of liver and/or bone metastases. In the comparative study in advanced breast cancer patients, CTC grade 3 or 4 elevation of gamma glutamyl transferase without documented evidence of liver metastasis was reported in 2.7% of patients treated with AROMASIN and in 1.8% of patients treated with megestrol acetate.

In patients with early breast cancer, elevations in bilirubin, alkaline phosphatase, and creatinine were more common in those receiving exemestane than either tamoxifen or placebo. Treatment-emergent bilirubin elevations (any CTC grade) occurred in 5% of exemestane patients and 0.8% of tamoxifen patients on the Intergroup Exemestane Study (IES), and in 7% of exemestane treated patients vs. 0% of placebo treated patients in the 027 study. CTC grade 3–4 increases in bilirubin occurred in 0.9% of exemestane treated patients compared to 0.1% of tamoxifen treated patients. Alkaline phosphatase elevations of any CTC grade occurred in 15% of exemestane treated patients on the IES compared to 2.6% of tamoxifen treated patients, and in 14% of exemestane treated patients compared to 7% of placebo treated patients in study 027. Creatinine elevations occurred in 6% of exemestane treated patients and 4.3% of tamoxifen treated patients on the IES and in 6% of exemestane treated patients and 0% of placebo treated patients in study 027.

5.5 Use in Premenopausal Women

AROMASIN is not indicated for the treatment of breast cancer in premenopausal women.

5.6 Embryo-Fetal Toxicity

Based on findings from animal studies and its mechanism of action, AROMASIN can cause fetal harm when administered to a pregnant woman. In animal reproduction studies, administration of exemestane to pregnant rats and rabbits caused increased incidence of abortions and embryo-fetal toxicity. Advise pregnant women of the potential risk to a fetus. Advise females of reproductive potential to use effective contraception during treatment with AROMASIN and for 1 month after the last dose [see Use in Specific Populations (8.1), (8.3) and Clinical Pharmacology (12.1)].

6 ADVERSE REACTIONS

The following clinically significant adverse reactions are described elsewhere in the labeling:

- Reductions in Bone Mineral Density (BMD) [see Warnings and Precautions (5.1)]

6.1 Clinical Trials Experience

Because clinical trials are conducted under widely varying conditions, adverse reaction rates observed in the clinical trials of a drug cannot be directly compared to rates in the clinical trials of another drug and may not reflect the rates observed in clinical practice.

Adjuvant Therapy

The data described below reflect exposure to AROMASIN in 2325 postmenopausal women with early breast cancer. AROMASIN tolerability in postmenopausal women with early breast cancer was evaluated in two well-controlled trials: the IES study [See Clinical Studies (14.1)] and the 027 study (a randomized, placebo-controlled, double-blind, parallel group study specifically designed to assess the effects of exemestane on bone metabolism, hormones, lipids, and coagulation factors over 2 years of treatment).

The median duration of adjuvant treatment was 27.4 months and 27.3 months for patients receiving AROMASIN or tamoxifen, respectively, within the IES study and 23.9 months for patients receiving AROMASIN or placebo within the 027 study. Median duration of observation after randomization for AROMASIN was 34.5 months and for tamoxifen was 34.6 months. Median duration of observation was 30 months for both groups in the 027 study.

Certain adverse reactions, which were expected based on the known pharmacological properties and side effect profiles of test drugs, were actively sought through a positive checklist. Signs and symptoms were graded for severity using CTC in both studies. Within the IES study, the presence of some illnesses/conditions was monitored through a positive checklist without assessment of severity. These included myocardial infarction, other cardiovascular disorders, gynecological disorders, osteoporosis, osteoporotic fractures, other primary cancer, and hospitalizations.

Within the IES study, discontinuations due to adverse reactions occurred in 6% and 5% of patients receiving AROMASIN and tamoxifen, respectively, and in 12% and 4.1% of patients receiving exemestane or placebo respectively within study 027.

Deaths due to any cause were reported for 1.3% of the exemestane treated patients and 1.4% of the tamoxifen treated patients within the IES study. There were 6 deaths due to stroke on the exemestane arm compared to 2 on tamoxifen. There were 5 deaths due to cardiac failure on the exemestane arm compared to 2 on tamoxifen.

The incidence of cardiac ischemic events (myocardial infarction, angina, and myocardial ischemia) was 1.6% in exemestane treated patients and 0.6% in tamoxifen treated patients in the IES study. Cardiac failure was observed in 0.4% of exemestane treated patients and 0.3% of tamoxifen treated patients.

In the adjuvant treatment of early breast cancer, the most common adverse reactions occurring in ≥10% of patients in any treatment group (AROMASIN vs. tamoxifen) were hot flushes (21% vs. 20%), fatigue (16% vs. 15%), arthralgia (15% vs. 9%), headache (13% vs. 11%), insomnia (12% vs. 9%), and increased sweating (12% vs. 10%). Discontinuation rates due to AEs were similar between AROMASIN and tamoxifen (6% vs. 5%). Incidences of cardiac ischemic events (myocardial infarction, angina, and myocardial ischemia) were AROMASIN 1.6%, tamoxifen 0.6%. Incidence of cardiac failure: AROMASIN 0.4%, tamoxifen 0.3%.

Treatment-emergent adverse reactions and illnesses including all causalities and occurring with an incidence of ≥5% in either treatment group of the IES study during or within one month of the end of treatment are shown in Table 2.

Table 2. Incidence (%) of Adverse Reactions of all Grades [Graded according to Common Toxicity Criteria;] and Illnesses Occurring in (≥5%) of Patients in Any Treatment Group in Study IES in Postmenopausal Women with Early Breast Cancer
 | % of patients
Body system and Adverse Reaction by MedDRA dictionary | AROMASIN 25 mg daily (N=2252) | Tamoxifen 20 mg daily [75 patients received tamoxifen 30 mg daily;] (N=2280)
Eye
Visual disturbances [Event actively sought.] | 5 | 3.8
Gastrointestinal
Nausea | 9 | 9
General Disorders
Fatigue | 16 | 15
Musculoskeletal
Arthralgia | 15 | 9
Pain in limb | 9 | 6
Back pain | 9 | 7
Osteoarthritis | 6 | 4.5
Nervous System
Headache | 13 | 11
Dizziness | 10 | 8
Psychiatric
Insomnia | 12 | 9
Depression | 6 | 6
Skin & Subcutaneous Tissue
Increased sweating | 12 | 10
Vascular
Hot flushes | 21 | 20
Hypertension | 10 | 8

In the IES study, as compared to tamoxifen, AROMASIN was associated with a higher incidence of events in musculoskeletal disorders and in nervous system disorders, including the following events occurring with frequency lower than 5% (osteoporosis [4.6% vs. 2.8%], osteochondrosis [0.3% vs. 0%] and stenosing tenosynovitis (trigger finger) [0.3% vs. 0%], paresthesia [2.6% vs. 0.9%], carpal tunnel syndrome [2.4% vs. 0.2%], and neuropathy [0.6% vs. 0.1%]). Diarrhea was also more frequent in the exemestane group (4.2% vs. 2.2%). Clinical fractures were reported in 94 patients receiving exemestane (4.2%) and 71 patients receiving tamoxifen (3.1%). After a median duration of therapy of about 30 months and a median follow-up of about 52 months, gastric ulcer was observed at a slightly higher frequency in the AROMASIN group compared to tamoxifen (0.7% vs. <0.1%). The majority of patients on AROMASIN with gastric ulcer received concomitant treatment with non-steroidal anti-inflammatory agents and/or had a prior history.

Tamoxifen was associated with a higher incidence of muscle cramps [3.1% vs. 1.5%], thromboembolism [2.0% vs. 0.9%], endometrial hyperplasia [1.7% vs. 0.6%], and uterine polyps [2.4% vs. 0.4%].

Common adverse reactions occurring in study 027 are described in Table 3.

Table 3. Incidence of Selected Treatment-Emergent Adverse Reactions of all CTC Grades [Most events were CTC grade 1–2] Occurring in ≥ 5% of Patients in Either Arm in Study 027
Adverse Reaction | Exemestane N=73 (% incidence) | Placebo N=73 (% incidence)
Hot flushes | 33 | 25
Arthralgia | 29 | 29
Increased sweating | 18 | 21
Alopecia | 15 | 4.1
Hypertension | 15 | 7
Insomnia | 14 | 15
Nausea | 12 | 16
Fatigue | 11 | 19
Abdominal pain | 11 | 14
Depression | 10 | 7
Diarrhea | 10 | 1.4
Dizziness | 10 | 10
Dermatitis | 8 | 1.4
Headache | 7 | 4.1
Myalgia | 6 | 4.1
Edema | 6 | 7

Treatment of Advanced Breast Cancer

A total of 1058 patients were treated with exemestane 25 mg once daily in the clinical trials program. One death was considered possibly related to treatment with exemestane; an 80-year-old woman with known coronary artery disease had a myocardial infarction with multiple organ failure after 9 weeks on study treatment. In the clinical trials program, 3% of the patients discontinued treatment with exemestane because of adverse reactions, 2.7% of patients discontinued exemestane within the first 10 weeks of treatment.

In the comparative study, adverse reactions were assessed for 358 patients treated with AROMASIN and 400 patients treated with megestrol acetate. Fewer patients receiving AROMASIN discontinued treatment because of adverse reactions than those treated with megestrol acetate (2% vs. 5%). Adverse reactions that were considered drug related or of indeterminate cause included hot flashes (13% vs. 5%), nausea (9% vs. 5%), fatigue (8% vs. 10%), increased sweating (4% vs. 8%), and increased appetite (3% vs. 6%) for AROMASIN and megestrol acetate, respectively. The proportion of patients experiencing an excessive weight gain (>10% of their baseline weight) was significantly higher with megestrol acetate than with AROMASIN (17% vs. 8%).

In the treatment of advanced breast cancer, the most common adverse reactions included hot flushes (13% vs. 5%), nausea (9% vs. 5%), fatigue (8% vs. 10%), increased sweating (4% vs. 8%), and increased appetite (3% vs. 6%) for AROMASIN and megestrol acetate, respectively.

Table 4 shows the adverse reactions of all CTC grades, regardless of causality, reported in 5% or greater of patients in the study treated either with AROMASIN or megestrol acetate.

Table 4. Incidence (%) of Adverse Reactions of all Grades [Graded according to Common Toxicity Criteria] and Causes Occurring in ≥5% of Advanced Breast Cancer Patients In Each Treatment Arm in the Comparative Study
Body system and Adverse Reaction by WHO ART dictionary | AROMASIN 25 mg once daily (N=358) | Megestrol Acetate 40 mg QID (N=400)
Autonomic Nervous
Increased sweating | 6 | 9
Body as a Whole
Fatigue | 22 | 29
Hot flashes | 13 | 6
Pain | 13 | 13
Influenza-like symptoms | 6 | 5
Edema (includes edema, peripheral edema, leg edema) | 7 | 6
Cardiovascular
Hypertension | 5 | 6
Nervous
Depression | 13 | 9
Insomnia | 11 | 9
Anxiety | 10 | 11
Dizziness | 8 | 6
Headache | 8 | 7
Gastrointestinal
Nausea | 18 | 12
Vomiting | 7 | 4
Abdominal pain | 6 | 11
Anorexia | 6 | 5
Constipation | 5 | 8
Diarrhea | 4 | 5
Increased appetite | 3 | 6
Respiratory
Dyspnea | 10 | 15
Coughing | 6 | 7

Adverse reactions of any cause (from 2% to 5%) reported in the comparative study for patients receiving AROMASIN 25 mg once daily were fever, generalized weakness, paresthesia, pathological fracture, bronchitis, sinusitis, rash, itching, urinary tract infection, and lymphedema.

Additional adverse reactions of any cause observed in the overall clinical trials program (N = 1058) in 5% or greater of patients treated with exemestane 25 mg once daily but not in the comparative study included pain at tumor sites (8%), asthenia (6%), and fever (5%). Adverse reactions of any cause reported in 2% to 5% of all patients treated with exemestane 25 mg in the overall clinical trials program but not in the comparative study included chest pain, hypoesthesia, confusion, dyspepsia, arthralgia, back pain, skeletal pain, infection, upper respiratory tract infection, pharyngitis, rhinitis, and alopecia.

6.2 Postmarketing Experience

The following adverse reactions have been identified during post approval use of AROMASIN. Because these reactions are reported voluntarily from a population of uncertain size, it is not always possible to reliably estimate their frequency or establish a causal relationship to drug exposure.

Immune system disorders- hypersensitivity

Hepatobiliary disorders- hepatitis including cholestatic hepatitis

Nervous system disorders- paresthesia

Musculoskeletal and connective tissue disorder- tendon disorders including tendon rupture, tendonitis, and tenosynovitis

Skin and subcutaneous tissue disorders- acute generalized exanthematous pustulosis, urticaria, pruritus

7 DRUG INTERACTIONS

Drugs That Induce CYP 3A4

Co-medications that induce CYP 3A4 (e.g., rifampicin, phenytoin, carbamazepine, phenobarbital, or St. John's wort) may significantly decrease exposure to exemestane. Dose modification is recommended for patients who are also receiving a strong CYP 3A4 inducer [see Dosage and Administration (2.2) and Clinical Pharmacology (12.3)].

8 USE IN SPECIFIC POPULATIONS

8.1 Pregnancy

Risk Summary

Based on findings in animal studies and its mechanism of action, AROMASIN can cause fetal harm when administered to a pregnant woman [see Clinical Pharmacology (12.1)]. Limited human data from case reports are insufficient to inform a drug-associated risk. In animal reproduction studies, administration of exemestane to pregnant rats and rabbits caused increased incidence of abortions, embryo-fetal toxicity, and prolonged gestation with abnormal or difficult labor [see Data]. Advise pregnant women of the potential risk to a fetus.

The estimated background risk of major birth defects and miscarriage for the indicated population is unknown. In the US general population, the estimated background risk of major birth defects and miscarriage in clinically recognized pregnancies is 2-4% and 15-20%, respectively.

Data

Animal Data

In animal reproduction studies in rats and rabbits, exemestane caused embryo-fetal toxicity, and was abortifacient. Radioactivity related to ^14C-exemestane crossed the placenta of rats following oral administration of 1 mg/kg exemestane. The concentration of exemestane and its metabolites was approximately equivalent in maternal and fetal blood. When rats were administered exemestane from 14 days prior to mating until either days 15 or 20 of gestation, and resuming for the 21 days of lactation, an increase in placental weight was seen at 4 mg/kg/day (approximately 1.5 times the recommended human daily dose on a mg/m^2 basis). Increased resorptions, reduced number of live fetuses, decreased fetal weight, retarded ossification, prolonged gestation and abnormal or difficult labor was observed at doses equal to or greater than 20 mg/kg/day (approximately 7.5 times the recommended human daily dose on a mg/m^2 basis). Daily doses of exemestane, given to rabbits during organogenesis, caused a decrease in placental weight at 90 mg/kg/day (approximately 70 times the recommended human daily dose on a mg/m^2 basis) and in the presence of maternal toxicity, abortions, an increase in resorptions, and a reduction in fetal body weight were seen at 270 mg/kg/day. No malformations were noted when exemestane was administered to pregnant rats or rabbits during the organogenesis period at doses up to 810 and 270 mg/kg/day, respectively (approximately 320 and 210 times the recommended human dose on a mg/m^2 basis, respectively).

8.2 Lactation

Risk Summary

There is no information on the presence of exemestane in human milk, or on its effects on the breastfed infant or milk production. Exemestane is present in rat milk at concentrations similar to maternal plasma [see Data]. Because of the potential for serious adverse reactions in breast-fed infants from AROMASIN, advise a woman not to breastfeed during treatment with AROMASIN and for 1 month after the final dose.

Data

Radioactivity related to exemestane appeared in rat milk within 15 minutes of oral administration of radiolabeled exemestane. Concentrations of exemestane and its metabolites were approximately equivalent in the milk and plasma of rats for 24 hours after a single oral dose of 1 mg/kg ^14C-exemestane.

8.3 Females and Males of Reproductive Potential

Pregnancy Testing

Pregnancy testing is recommended for females of reproductive potential within seven days prior to initiating AROMASIN.

Contraception

Females

AROMASIN can cause fetal harm when administered to a pregnant woman [see Use in Specific Populations (8.1)]. Advise females of reproductive potential to use effective contraception during treatment with AROMASIN and for 1 month after the final dose.

Infertility

Based on findings in animals, male and female fertility may be impaired by treatment with AROMASIN [see Nonclinical Toxicology (13.1)].

8.4 Pediatric Use

Safety and effectiveness in pediatric patients have not been established.

8.6 Hepatic Impairment

The AUC of exemestane was increased in subjects with moderate or severe hepatic impairment (Childs-Pugh B or C) [see Clinical Pharmacology (12.3)]. However, based on experience with exemestane at repeated doses up to 200 mg daily that demonstrated a moderate increase in non life-threatening adverse reactions, dosage adjustment does not appear to be necessary.

8.7 Renal Impairment

The AUC of exemestane was increased in subjects with moderate or severe renal impairment (creatinine clearance <35 mL/min/1.73 m^2) [see Clinical Pharmacology (12.3)]. However, based on experience with exemestane at repeated doses up to 200 mg daily that demonstrated a moderate increase in non life-threatening adverse reactions, dosage adjustment does not appear to be necessary.

10 OVERDOSAGE

Clinical trials have been conducted with exemestane given as a single dose to healthy female volunteers at doses as high as 800 mg and daily for 12 weeks to postmenopausal women with advanced breast cancer at doses as high as 600 mg. These dosages were well tolerated. There is no specific antidote to overdosage and treatment must be symptomatic. General supportive care, including frequent monitoring of vital signs and close observation of the patient, is indicated.

A male child (age unknown) accidentally ingested a 25-mg tablet of exemestane. The initial physical examination was normal, but blood tests performed 1 hour after ingestion indicated leucocytosis (WBC 25000/mm^3 with 90% neutrophils). Blood tests were repeated 4 days after the incident and were normal. No treatment was given.

In mice, mortality was observed after a single oral dose of exemestane of 3200 mg/kg, the lowest dose tested (about 640 times the recommended human dose on a mg/m^2 basis). In rats and dogs, mortality was observed after single oral doses of exemestane of 5000 mg/kg (about 2000 times the recommended human dose on a mg/m^2 basis) and of 3000 mg/kg (about 4000 times the recommended human dose on a mg/m^2 basis), respectively.

Convulsions were observed after single doses of exemestane of 400 mg/kg and 3000 mg/kg in mice and dogs (approximately 80 and 4000 times the recommended human dose on a mg/m^2 basis), respectively.

11 DESCRIPTION

AROMASIN® Tablets for oral administration contain 25 mg of exemestane, an irreversible, steroidal aromatase inactivator. Exemestane is chemically described as 6-methylenandrosta-1,4-diene-3,17-dione. Its molecular formula is C20H24O2 and its structural formula is as follows:

The active ingredient is a white to slightly yellow crystalline powder with a molecular weight of 296.41. Exemestane is freely soluble in N, N-dimethylformamide, soluble in methanol, and practically insoluble in water.

Each AROMASIN Tablet contains the following inactive ingredients: mannitol, crospovidone, polysorbate 80, hypromellose, colloidal silicon dioxide, microcrystalline cellulose, sodium starch glycolate, magnesium stearate, simethicone, polyethylene glycol 6000, sucrose, magnesium carbonate, titanium dioxide, methylparaben, and polyvinyl alcohol.

12 CLINICAL PHARMACOLOGY

12.1 Mechanism of Action

Breast cancer cell growth may be estrogen-dependent. Aromatase is the principal enzyme that converts androgens to estrogens both in pre- and postmenopausal women. While the main source of estrogen (primarily estradiol) is the ovary in premenopausal women, the principal source of circulating estrogens in postmenopausal women is from conversion of adrenal and ovarian androgens (androstenedione and testosterone) to estrogens (estrone and estradiol) by the aromatase enzyme in peripheral tissues.

Exemestane is an irreversible, steroidal aromatase inactivator, structurally related to the natural substrate androstenedione. It acts as a false substrate for the aromatase enzyme, and is processed to an intermediate that binds irreversibly to the active site of the enzyme, causing its inactivation, an effect also known as "suicide inhibition." Exemestane significantly lowers circulating estrogen concentrations in postmenopausal women, but has no detectable effect on adrenal biosynthesis of corticosteroids or aldosterone. Exemestane has no effect on other enzymes involved in the steroidogenic pathway up to a concentration at least 600 times higher than that inhibiting the aromatase enzyme.

12.2 Pharmacodynamics

Effect on Estrogens

Multiple doses of exemestane ranging from 0.5 to 600 mg/day were administered to postmenopausal women with advanced breast cancer. Plasma estrogen (estradiol, estrone, and estrone sulfate) suppression was seen starting at a 5-mg daily dose of exemestane, with a maximum suppression of at least 85% to 95% achieved at a 25-mg dose. Exemestane 25 mg daily reduced whole body aromatization (as measured by injecting radiolabeled androstenedione) by 98% in postmenopausal women with breast cancer. After a single dose of exemestane 25 mg, the maximal suppression of circulating estrogens occurred 2 to 3 days after dosing and persisted for 4 to 5 days.

Effect on Corticosteroids

In multiple-dose trials of doses up to 200 mg daily, exemestane selectivity was assessed by examining its effect on adrenal steroids. Exemestane did not affect cortisol or aldosterone secretion at baseline or in response to ACTH at any dose. Thus, no glucocorticoid or mineralocorticoid replacement therapy is necessary with exemestane treatment.

Other Endocrine Effects

Exemestane does not bind significantly to steroidal receptors, except for a slight affinity for the androgen receptor (0.28% relative to dihydrotestosterone). The binding affinity of its 17-dihydrometabolite for the androgen receptor, however, is 100 times that of the parent compound. Daily doses of exemestane up to 25 mg had no significant effect on circulating levels of androstenedione, dehydroepiandrosterone sulfate, or 17-hydroxyprogesterone, and were associated with small decreases in circulating levels of testosterone. Increases in testosterone and androstenedione levels have been observed at daily doses of 200 mg or more. A dose-dependent decrease in sex hormone binding globulin (SHBG) has been observed with daily exemestane doses of 2.5 mg or higher. Slight, nondose-dependent increases in serum luteinizing hormone (LH) and follicle-stimulating hormone (FSH) levels have been observed even at low doses as a consequence of feedback at the pituitary level. Exemestane 25 mg daily had no significant effect on thyroid function [free triiodothyronine (FT3), free thyroxine (FT4), and thyroid stimulating hormone (TSH)].

Coagulation and Lipid Effects

In study 027 of postmenopausal women with early breast cancer treated with exemestane (N=73) or placebo (N=73), there was no change in the coagulation parameters activated partial thromboplastin time [APTT], prothrombin time [PT], and fibrinogen. Plasma HDL cholesterol was decreased 6–9% in exemestane treated patients; total cholesterol, LDL cholesterol, triglycerides, apolipoprotein-A1, apolipoprotein-B, and lipoprotein-a were unchanged. An 18% increase in homocysteine levels was also observed in exemestane treated patients compared with a 12% increase seen with placebo.

12.3 Pharmacokinetics

Following oral administration to healthy postmenopausal women, plasma concentrations of exemestane decline polyexponentially with a mean terminal half-life of about 24 hours. The pharmacokinetics of exemestane are dose proportional after single (10 to 200 mg) or repeated oral doses (0.5 to 50 mg). Following repeated daily doses of exemestane 25 mg, plasma concentrations of unchanged drug are similar to levels measured after a single dose. Pharmacokinetic parameters in postmenopausal women with advanced breast cancer following single or repeated doses have been compared with those in healthy, postmenopausal women. After repeated dosing, the average oral clearance in women with advanced breast cancer was 45% lower than the oral clearance in healthy postmenopausal women, with corresponding higher systemic exposure. Mean AUC values following repeated doses in women with breast cancer (75.4 ng∙h/mL) were about twice those in healthy women (41.4 ng∙h/mL).

Absorption

Following oral administration, exemestane appeared to be absorbed more rapidly in women with breast cancer than in the healthy women, with a mean tmax of 1.2 hours in the women with breast cancer and 2.9 hours in healthy women. Approximately 42% of radiolabeled exemestane was absorbed from the gastrointestinal tract. A high-fat breakfast increased AUC and Cmax of exemestane by 59% and 39%, respectively, compared to fasted state.

Distribution

Exemestane is distributed extensively into tissues. Exemestane is 90% bound to plasma proteins and the fraction bound is independent of the total concentration. Albumin and α11-acid glycoprotein both contribute to the binding. The distribution of exemestane and its metabolites into blood cells is negligible.

Metabolism

Exemestane is extensively metabolized, with levels of the unchanged drug in plasma accounting for less than 10% of the total radioactivity. The initial steps in the metabolism of exemestane are oxidation of the methylene group in position 6 and reduction of the 17-keto group with subsequent formation of many secondary metabolites. Each metabolite accounts only for a limited amount of drug-related material. The metabolites are inactive or inhibit aromatase with decreased potency compared with the parent drug. One metabolite may have androgenic activity [see Clinical Pharmacology (12.2)]. Studies using human liver preparations indicate that cytochrome P 450 3A4 (CYP 3A4) is the principal isoenzyme involved in the oxidation of exemestane. Exemestane is metabolized also by aldoketoreductases.

Elimination

Following administration of radiolabeled exemestane to healthy postmenopausal women, the cumulative amounts of radioactivity excreted in urine and feces were similar (42 ± 3% in urine and 42 ± 6% in feces over a 1-week collection period). The amount of drug excreted unchanged in urine was less than 1% of the dose.

Specific Populations

Geriatric: Healthy postmenopausal women aged 43 to 68 years were studied in the pharmacokinetic trials. Age-related alterations in exemestane pharmacokinetics were not seen over this age range.

Gender: The pharmacokinetics of exemestane following administration of a single, 25-mg tablet to fasted healthy males (mean age 32 years) were similar to the pharmacokinetics of exemestane in fasted healthy postmenopausal women (mean age 55 years).

Race: The influence of race on exemestane pharmacokinetics has not been evaluated.

Hepatic Impairment: The pharmacokinetics of exemestane have been investigated in subjects with moderate or severe hepatic impairment (Childs-Pugh B or C). Following a single 25-mg oral dose, the AUC of exemestane was approximately 3 times higher than that observed in healthy volunteers.

Renal Impairment: The AUC of exemestane after a single 25-mg dose was approximately 3 times higher in subjects with moderate or severe renal insufficiency (creatinine clearance <35 mL/min/1.73 m^2) compared with the AUC in healthy volunteers.

Pediatric: The pharmacokinetics of exemestane have not been studied in pediatric patients.

Drug Interaction Studies

Exemestane does not inhibit any of the major CYP isoenzymes, including CYP 1A2, 2C9, 2D6, 2E1, and 3A4.

In a pharmacokinetic interaction study of 10 healthy postmenopausal volunteers pretreated with potent CYP 3A4 inducer rifampicin 600 mg daily for 14 days followed by a single dose of exemestane 25 mg, the mean plasma Cmax and AUC 0–∞ of exemestane were decreased by 41% and 54%, respectively [see Dosage and Administration (2.2) and Drug Interactions (7)].

In a clinical pharmacokinetic study, coadministration of ketoconazole, a potent inhibitor of CYP 3A4, has no significant effect on exemestane pharmacokinetics. Although no other formal drug-drug interaction studies with inhibitors have been conducted, significant effects on exemestane clearance by CYP isoenzyme inhibitors appear unlikely.

13 NONCLINICAL TOXICOLOGY

13.1 Carcinogenesis, Mutagenesis, Impairment of Fertility

A 2-year carcinogenicity study in mice at doses of 50, 150, and 450 mg/kg/day exemestane (gavage), resulted in an increased incidence of hepatocellular adenomas and/or carcinomas in both genders at the high dose level. Plasma AUC (0–24hr) at the high dose were 2575 ± 386 and 5667 ± 1833 ng.hr/mL in males and females (approx. 34 and 75 fold the AUC in postmenopausal patients at the recommended clinical dose). An increased incidence of renal tubular adenomas was observed in male mice at the high dose of 450 mg/kg/day. Since the doses tested in mice did not achieve an MTD, neoplastic findings in organs other than liver and kidneys remain unknown.

A separate carcinogenicity study was conducted in rats at the doses of 30, 100, and 315 mg/kg/day exemestane (gavage) for 92 weeks in males and 2 years in females. No evidence of carcinogenic activity up to the highest dose tested of 315 mg/kg/day was observed in females. The male rat study was inconclusive since it was terminated prematurely at Week 92. At the highest dose, plasma AUC(0–24hr) levels in male (1418 ± 287 ng.hr/mL) and female (2318 ± 1067 ng.hr/mL) rats were 19 and 31 fold higher than those measured in postmenopausal cancer patients receiving the recommended clinical dose.

Exemestane was not mutagenic in vitro in bacteria (Ames test) or mammalian cells (V79 Chinese hamster lung cells). Exemestane was clastogenic in human lymphocytes in vitro without metabolic activation but was not clastogenic in vivo (micronucleus assay in mouse bone marrow). Exemestane did not increase unscheduled DNA synthesis in rat hepatocytes when tested in vitro.

In a pilot reproductive study in rats, male rats were treated with doses of 125–1000 mg/kg/day exemestane, beginning 63 days prior to and during cohabitation. Untreated female rats showed reduced fertility when mated to males treated with ≥500 mg/kg/day exemestane (≥200 times the recommended human dose on a mg/m^2 basis). In a separate study, exemestane was given to female rats at 4–100 mg/kg/day beginning 14 days prior to mating and through day 15 or 20 of gestation. Exemestane increased the placental weights at ≥4 mg/kg/day (≥1.5 times the human dose on a mg/m^2 basis). Exemestane showed no effects on ovarian function, mating behavior, and conception rate in rats given doses up to 20 mg/kg/day (approximately 8 times the recommended human dose on a mg/m^2 basis); however, decreases in mean litter size and fetal body weight, along with delayed ossification were evidenced at ≥20 mg/kg/day. In general toxicology studies, changes in the ovary, including hyperplasia, an increase in the incidence of ovarian cysts, and a decrease in corpora lutea were observed with variable frequency in mice, rats, and dogs at doses that ranged from 3–20 times the human dose on a mg/m^2 basis.

14 CLINICAL STUDIES

14.1 Adjuvant Treatment in Early Breast Cancer

The Intergroup Exemestane Study 031 (IES) was a randomized, double-blind, multicenter, multinational study comparing exemestane (25 mg/day) vs. tamoxifen (20 or 30 mg/day) in postmenopausal women with early breast cancer. Patients who remained disease-free after receiving adjuvant tamoxifen therapy for 2 to 3 years were randomized to receive an additional 3 or 2 years of AROMASIN or tamoxifen to complete a total of 5 years of hormonal therapy.

The primary objective of the study was to determine whether, in terms of disease-free survival, it was more effective to switch to AROMASIN rather than continuing tamoxifen therapy for the remainder of five years. Disease-free survival was defined as the time from randomization to time of local or distant recurrence of breast cancer, contralateral invasive breast cancer, or death from any cause.

The secondary objectives were to compare the two regimens in terms of overall survival and long-term tolerability. Time to contralateral invasive breast cancer and distant recurrence-free survival were also evaluated.

A total of 4724 patients in the intent-to-treat (ITT) analysis were randomized to AROMASIN (exemestane tablets) 25 mg once daily (N = 2352) or to continue to receive tamoxifen once daily at the same dose received before randomization (N = 2372). Demographics and baseline tumor characteristics are presented in Table 5. Prior breast cancer therapy is summarized in Table 6.

Table 5. Demographic and Baseline Tumor Characteristics from the IES Study of Postmenopausal Women with Early Breast Cancer (ITT Population)
Parameter | Exemestane (N = 2352) | Tamoxifen (N = 2372)
Age (years):
Median age (range) | 63.0 (38.0 – 96.0) | 63.0 (31.0 – 90.0)
Race, n (%):
Caucasian | 2315 (98.4) | 2333 (98.4)
Hispanic | 13 (0.6) | 13 (0.5)
Asian | 10 (0.4) | 9 (0.4)
Black | 7 (0.3) | 10 (0.4)
Other/not reported | 7 (0.3) | 7 (0.3)
Nodal status, n (%):
Negative | 1217 (51.7) | 1228 (51.8)
Positive | 1051 (44.7) | 1044 (44.0)
1–3 Positive nodes | 721 (30.7) | 708 (29.8)
4–9 Positive nodes | 239 (10.2) | 244 (10.3)
>9 Positive nodes | 88 (3.7) | 86 (3.6)
Not reported | 3 (0.1) | 6 (0.3)
Unknown or missing | 84 (3.6) | 100 (4.2)
Histologic type, n (%):
Infiltrating ductal | 1777 (75.6) | 1830 (77.2)
Infiltrating lobular | 341 (14.5) | 321 (13.5)
Other | 231 (9.8) | 213 (9.0)
Unknown or missing | 3 (0.1) | 8 (0.3)
Receptor status [Results for receptor status include the results of the post-randomization testing of specimens from subjects for whom receptor status was unknown at randomization.] , n (%):
ER and PgR Positive | 1331 (56.6) | 1319 (55.6)
ER Positive and PgR Negative/Unknown | 677 (28.8) | 692 (29.2)
ER Unknown and PgR Positive [Only one subject in the exemestane group had unknown ER status and positive PgR status.] /Unknown | 288 (12.2) | 291 (12.3)
ER Negative and PgR Positive | 6 (0.3) | 7 (0.3)
ER Negative and PgR Negative/Unknown (none positive) | 48 (2.0) | 58 (2.4)
Missing | 2 (0.1) | 5 (0.2)
Tumor Size, n (%):
≤ 0.5 cm | 58 (2.5) | 46 (1.9)
> 0.5 – 1.0 cm | 315 (13.4) | 302 (12.7)
> 1.0 – 2 cm | 1031 (43.8) | 1033 (43.5)
> 2.0 – 5.0 cm | 833 (35.4) | 883 (37.2)
> 5.0 cm | 62 (2.6) | 59 (2.5)
Not reported | 53 (2.3) | 49 (2.1)
Tumor Grade, n (%):
G1 | 397 (16.9) | 393 (16.6)
G2 | 977 (41.5) | 1007 (42.5)
G3 | 454 (19.3) | 428 (18.0)
G4 | 23 (1.0) | 19 (0.8)
Unknown/Not Assessed/Not reported | 501 (21.3) | 525 (22.1)

Table 6. Prior Breast Cancer Therapy of Patients in the IES Study of Postmenopausal Women with Early Breast Cancer (ITT Population)
Parameter | Exemestane (N = 2352) | Tamoxifen (N = 2372)
Type of surgery, n (%):
Mastectomy | 1232 (52.4) | 1242 (52.4)
Breast-conserving | 1116 (47.4) | 1123 (47.3)
Unknown or missing | 4 (0.2) | 7 (0.3)
Radiotherapy to the breast, n (%):
Yes | 1524 (64.8) | 1523 (64.2)
No | 824 (35.5) | 843 (35.5)
Not reported | 4 (0.2) | 6 (0.3)
Prior therapy, n (%):
Chemotherapy | 774 (32.9) | 769 (32.4)
Hormone replacement therapy | 567 (24.1) | 561 (23.7)
Bisphosphonates | 43 (1.8) | 34 (1.4)
Duration of tamoxifen therapy at randomization (months):
Median (range) | 28.5 (15.8 – 52.2) | 28.4 (15.6 – 63.0)
Tamoxifen dose, n (%):
20 mg | 2270 (96.5) | 2287 (96.4)
30 mg [The 30 mg dose was used only in Denmark, where this dose was the standard of care.] | 78 (3.3) | 75 (3.2)
Not reported | 4 (0.2) | 10 (0.4)

After a median duration of therapy of 27 months and with a median follow-up of 34.5 months, 520 events were reported, 213 in the AROMASIN group and 307 in the tamoxifen group (Table 7).

Table 7. Primary Endpoint Events (ITT Population)
Event | First Events N (%)
 | Exemestane (N = 2352) | Tamoxifen (N = 2372)
Loco-regional recurrence | 34 (1.45) | 45 (1.90)
Distant recurrence | 126 (5.36) | 183 (7.72)
Second primary – contralateral breast cancer | 7 (0.30) | 25 (1.05)
Death – breast cancer | 1 (0.04) | 6 (0.25)
Death – other reason | 41 (1.74) | 43 (1.81)
Death – missing/unknown | 3 (0.13) | 5 (0.21)
Ipsilateral breast cancer | 1 (0.04) | 0
Total number of events | 213 (9.06) | 307 (12.94)

Disease-free survival in the intent-to-treat population was statistically significantly improved [Hazard Ratio (HR) = 0.69, 95% CI: 0.58, 0.82, P = 0.00003, Table 8, Figure 1] in the AROMASIN arm compared to the tamoxifen arm. In the hormone receptor-positive subpopulation representing about 85% of the trial patients, disease-free survival was also statistically significantly improved (HR = 0.65, 95% CI: 0.53, 0.79, P = 0.00001) in the AROMASIN arm compared to the tamoxifen arm. Consistent results were observed in the subgroups of patients with node negative or positive disease, and patients who had or had not received prior chemotherapy.

An overall survival update at 119 months median follow-up showed no significant difference between the two groups, with 467 deaths (19.9%) occurring in the AROMASIN group and 510 deaths (21.5%) in the tamoxifen group.

Table 8. Efficacy Results from the IES Study in Postmenopausal Women with Early Breast Cancer
ITT Population | Hazard Ratio (95% CI) | p-value (log-rank test)
Disease-free survival | 0.69 (0.58–0.82) | 0.00003
Time to contralateral breast cancer | 0.32 (0.15–0.72) | 0.00340
Distant recurrence-free survival | 0.74 (0.62–0.90) | 0.00207
Overall survival | 0.91 (0.81–1.04) | 0.16 [Not adjusted for multiple testing.]
ER and/or PgR positive
Disease-free survival | 0.65 (0.53–0.79) | 0.00001
Time to contralateral breast cancer | 0.22 (0.08–0.57) | 0.00069
Distant recurrence-free survival | 0.73 (0.59–0.90) | 0.00367
Overall survival | 0.89 (0.78–1.02) | 0.09065

Figure 1. Disease-Free Survival in the IES Study of Postmenopausal Women with Early Breast Cancer (ITT Population)

14.2 Treatment of Advanced Breast Cancer

Exemestane 25 mg administered once daily was evaluated in a randomized double-blind, multicenter, multinational comparative study and in two multicenter single-arm studies of postmenopausal women with advanced breast cancer who had disease progression after treatment with tamoxifen for metastatic disease or as adjuvant therapy. Some patients also have received prior cytotoxic therapy, either as adjuvant treatment or for metastatic disease.

The primary purpose of the three studies was evaluation of objective response rate (complete response [CR] and partial response [PR]). Time to tumor progression and overall survival were also assessed in the comparative trial. Response rates were assessed based on World Health Organization (WHO) criteria, and in the comparative study, were submitted to an external review committee that was blinded to patient treatment. In the comparative study, 769 patients were randomized to receive AROMASIN (exemestane tablets) 25 mg once daily (N = 366) or megestrol acetate 40 mg four times daily (N = 403). Demographics and baseline characteristics are presented in Table 9.

Table 9. Demographics and Baseline Characteristics from the Comparative Study of Postmenopausal Women with Advanced Breast Cancer Whose Disease Had Progressed after Tamoxifen Therapy
Parameter | AROMASIN (N = 366) | Megestrol Acetate (N = 403)
Median Age (range) | 65 (35–89) | 65 (30–91)
ECOG Performance Status
0 | 167 (46%) | 187 (46%)
1 | 162 (44%) | 172 (43%)
2 | 34 (9%) | 42 (10%)
Receptor Status
ER and/or PgR + | 246 (67%) | 274 (68%)
ER and PgR unknown | 116 (32%) | 128 (32%)
Responders to prior tamoxifen | 68 (19%) | 85 (21%)
NE for response to prior tamoxifen | 46 (13%) | 41 (10%)
Site of Metastasis
Visceral ± other sites | 207 (57%) | 239 (59%)
Bone only | 61 (17%) | 73 (18%)
Soft tissue only | 54 (15%) | 51 (13%)
Bone & soft tissue | 43 (12%) | 38 (9%)
Measurable Disease | 287 (78%) | 314 (78%)
Prior Tamoxifen Therapy
Adjuvant or Neoadjuvant | 145 (40%) | 152 (38%)
Advanced Disease, Outcome
CR, PR, or SD ≥ 6 months | 179 (49%) | 210 (52%)
SD < 6 months, PD or NE | 42 (12%) | 41 (10%)
Prior Chemotherapy
For advanced disease ± adjuvant | 58 (16%) | 67 (17%)
Adjuvant only | 104 (28%) | 108 (27%)
No chemotherapy | 203 (56%) | 226 (56%)

The efficacy results from the comparative study are shown in Table 10. The objective response rates observed in the two treatment arms showed that AROMASIN was not different from megestrol acetate. Response rates for AROMASIN from the two single-arm trials were 23.4% and 28.1%.

Table 10. Efficacy Results from the Comparative Study of Postmenopausal Women with Advanced Breast Cancer Whose Disease Had Progressed after Tamoxifen Therapy
Response Characteristics | AROMASIN (N=366) | Megestrol Acetate (N=403)
Objective Response Rate = CR + PR (%) | 15.0 | 12.4
Difference in Response Rate (AR-MA) | 2.6
95% C.I. | 7.5, -2.3
CR (%) | 2.2 | 1.2
PR (%) | 12.8 | 11.2
SD ≥ 24 Weeks (%) | 21.3 | 21.1
Median Duration of Response (weeks) | 76.1 | 71.0
Median TTP (weeks) | 20.3 | 16.6
Hazard Ratio (AR-MA) | 0.84
Abbreviations: CR = complete response, PR = partial response, SD = stable disease (no change), TTP = time to tumor progression, C.I. = confidence interval, MA = megestrol acetate, AR = AROMASIN

There were too few deaths occurring across treatment groups to draw conclusions on overall survival differences. The Kaplan-Meier curve for time to tumor progression in the comparative study is shown in Figure 2.

Figure 2. Time to Tumor Progression in the Comparative Study of Postmenopausal Women With Advanced Breast Cancer Whose Disease Had Progressed After Tamoxifen Therapy

16 HOW SUPPLIED/STORAGE AND HANDLING

AROMASIN Tablets are round, biconvex, and off-white to slightly gray. Each tablet contains 25 mg of exemestane. The tablets are printed on one side with the number "7663" in black.

AROMASIN is packaged in HDPE bottles with a child-resistant screw cap, supplied in packs of 30 tablets.

30-tablet HDPE bottle | NDC 0009-7663-04

STORAGE AND HANDLING

Store at 25°C (77ºF); excursions permitted to 15°–30°C (59°–86°F) [see USP Controlled Room Temperature].

17 PATIENT COUNSELING INFORMATION

Advise the patient to read the FDA-approved patient labeling (Patient Information).

Bone Effects

Advise patients that AROMASIN lowers the level of estrogen in the body. This may lead to reduction in bone mineral density (BMD) over time. The lower the BMD, the greater the risk of osteoporosis and fracture [see Warnings and Precautions (5.1)].

Other Estrogen-Containing Agents

Advise patients that they should not take estrogen-containing agents while they are taking AROMASIN as these could interfere with its pharmacologic action [see Warnings and Precautions (5.3)].

Use in Premenopausal Women

Advise patients that AROMASIN is not for use for the treatment of breast cancer in premenopausal women [see Warnings and Precautions (5.5)].

Embryo-Fetal Toxicity

Advise pregnant women and females of reproductive potential that exposure during pregnancy or within 1 month prior to conception can result in fetal harm. Advise females to inform their healthcare provider of a known or suspected pregnancy [see Warnings and Precautions (5.6) and Use in Specific Populations (8.1)].

Advise females of reproductive potential to use effective contraception while taking AROMASIN and for 1 month after the last dose [see Use in Specific Populations (8.3)].

Lactation

Advise women not to breastfeed during treatment with AROMASIN and for 1 month after the last dose [see Use in Specific Populations (8.2)].

LAB-0098-22.0

Patient Information
AROMASIN® (ah ROME ah sin)
(exemestane) tablets

What is AROMASIN?

AROMASIN is used in women who are past menopause for the treatment of:

- Early breast cancer (cancer that has not spread outside the breast) in women who:
  - have cancer that needs the female hormone estrogen to grow, and
  - have had other treatments for breast cancer, and
  - have taken tamoxifen for 2 to 3 years, and
  - are switching to AROMASIN to complete 5 years in a row of hormonal therapy.
- Advanced breast cancer (cancer that has spread) after treatment with tamoxifen, and it did not work or is no longer working.

It is not known if AROMASIN is safe and effective in children.

Do not take AROMASIN if you are allergic to AROMASIN or any of the ingredients in AROMASIN. See the end of this leaflet for a complete list of ingredients in AROMASIN.

Before you take AROMASIN, tell your doctor about all your medical conditions, including if you:

- are still having menstrual periods (are not past menopause). AROMASIN is only for women who are past menopause.
- have weak or brittle bones (osteoporosis)
- are pregnant or plan to become pregnant. Taking AROMASIN during pregnancy or within 1 month of becoming pregnant can harm your unborn baby.
  - Females who are able to become pregnant should have a pregnancy test within 7 days before starting treatment with AROMASIN.
  - Females who are able to become pregnant should use effective birth control (contraceptive) during treatment with AROMASIN and for 1 month after your last dose of AROMASIN. Tell your doctor right away if you become pregnant or think you may be pregnant.
- are breastfeeding or plan to breastfeed. It is not known if AROMASIN passes into your breast milk. Do not breast-feed during treatment with AROMASIN and for 1 month after your last dose of AROMASIN.
- Have liver or kidney problems.

Tell your doctor about all the medicines you take, including prescription and over-the-counter medicines, vitamins and herbal supplements. Especially tell your doctor if you take medicines that contain estrogen, including other hormone replacement therapy or birth control pills or patches. AROMASIN should not be taken with medicines that contain estrogen as they could affect how well AROMASIN works.

How should I take AROMASIN?

- Take AROMASIN exactly as your doctor tells you.
- Take AROMASIN 1 time each day after a meal.
- If you take too much AROMASIN, call your doctor right away or go to nearest hospital emergency room.

What are the possible side effects of AROMASIN?

AROMASIN may cause serious side effects, including:

- Bone loss. AROMASIN decreases the amount of estrogen in your body which may reduce your bone mineral density (BMD) over time. This may increase your risk for bone fractures or weak and brittle bones (osteoporosis). Your doctor may check your bones during treatment with AROMASIN if you have osteoporosis or at risk for osteoporosis.

The most common side effects of AROMASIN in women with early breast cancer include:

- hot flashes
- headache

- feeling tired
- trouble sleeping

- joint pain
- increased sweating

The most common side effects of AROMASIN in women with advanced breast cancer include:

- hot flashes
- increased sweating

- nausea
- increased appetite

- feeling tired

Your doctor will do blood tests to check your vitamin D level before starting treatment with AROMASIN.

AROMASIN may cause decreased fertility in males and females. Talk to your doctor if you have concerns about fertility.

These are not all the possible side effects of AROMASIN. Call your doctor for medical advice about side effects. You may report side effects to FDA at 1-800-FDA-1088.

How should I store AROMASIN?

- Store AROMASIN at room temperature 68°F to 77°F (20°C to 25°C).
- Keep AROMASIN and all medicines out of the reach of children.

General information about the safe and effective use of AROMASIN.

Medicines are sometimes prescribed for purposes other than those listed in a Patient Information leaflet. Do not use AROMASIN for a condition for which it was not prescribed. Do not give AROMASIN to other people, even if they have the same symptoms you have. It may harm them. You can ask your pharmacist or doctor for information about AROMASIN that is written for health professionals.

What is in AROMASIN?

Active ingredient: exemestane

Inactive ingredients: mannitol, crospovidone, polysorbate 80, hypromellose, colloidal silicon dioxide, microcrystalline cellulose, sodium starch glycolate, magnesium stearate, simethicone, polyethylene glycol 6000, sucrose, magnesium carbonate, titanium dioxide, methylparaben, and polyvinyl alcohol.

LAB-0399-10.0

For more information, go to www.AROMASIN.com or call 1-888-AROMASIN (1-888-276-6274).

This Patient Information has been approved by the U.S. Food and Drug Administration Revised: 12/2024

PRINCIPAL DISPLAY PANEL - 25 mg Tablet Bottle Label

NDC 0009-7663-04
Pfizer

Aromasin®
exemestane tablets

25 mg

30 Tablets

Rx only